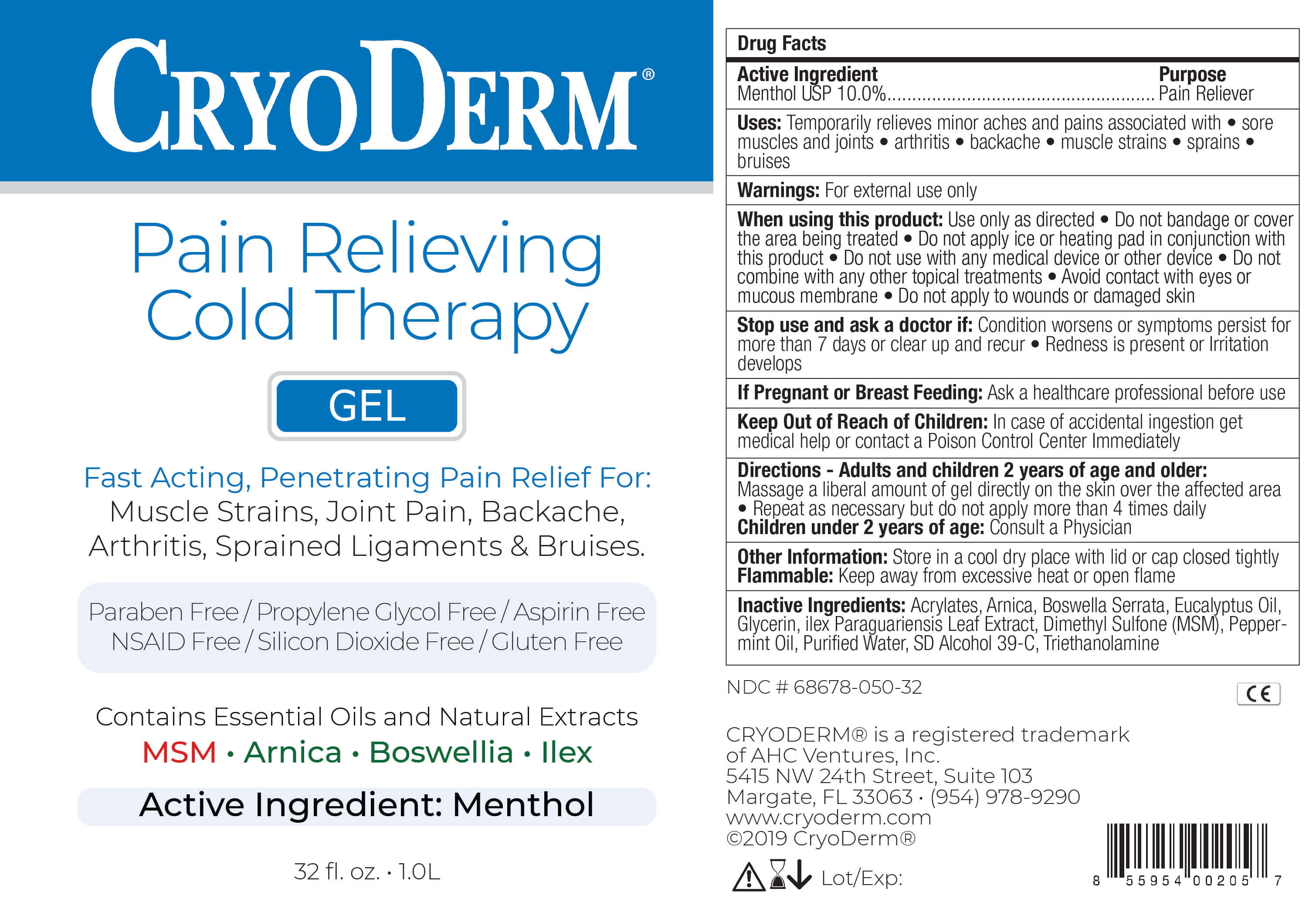 DRUG LABEL: Pain Relieving Cold Therapy
NDC: 68678-050 | Form: GEL
Manufacturer: AHC VENTURES CORP DBA CRYODERM
Category: otc | Type: HUMAN OTC DRUG LABEL
Date: 20250902

ACTIVE INGREDIENTS: MENTHOL 10 g/100 L
INACTIVE INGREDIENTS: GLYCERIN; ILEX PARAGUARIENSIS LEAF; PEPPERMINT OIL; (C10-C30)ALKYL METHACRYLATE ESTER; BOSWELLIA SERRATA WHOLE; ARNICA MONTANA FLOWER; EUCALYPTUS OIL; WATER; ALCOHOL; TROLAMINE; DIMETHYL SULFONE

Pain Relieving Cold Therapy

Active Ingredient

Menthol USP 10.0%

Purpose

Pain Reliever

Uses

Temporarily relieves minor minor aches and pains associated with

- sore musclkes and joints
- arthritis
- backache
- muscle strains
- sprains
- bruises

Warnings

For external use only

When using this product

Use only as directed

Do not bandage or cover the area being treated

Do not apply ice or heating pad in conjunction with this product

Do not use with any medical device or any other device

Do not combine with any other topical treatments

Avoid contact with eyes or mucous membrane

Do not apply to wounds or damaged skin

Stop use and ask a doctor if:

Conditions worsens or symptoms persist for more than 7 days or clear up and recur

- Redness if present or irritation develops

If Pregnant or Breast Feeding

Ask a healthcare professional before use

Keep Out of Reach of Children

In case of accidental ingestion get medical help or contact a Poison Control Center immediately

Directions - Adults and children 2 years of age and older

Massage a liberal amount of gel directly on the skin over the affected area

- Repeat as necessary but do not apply more than 4 times daily

Children under 2 years of age: Consult a physician

Other information

Store in a cool dry place with lid or cap closed tightly

Flammable: Keep away from excessive heat or open flame

Inactive Ingredients

Acrylates, Arnica, Boswella Serrata, Eucalyptus Oil, Glycerin, Ilex Paraguariensis Leaf Extract, Dimethyl Sulfone(MSM), Peppermint Oil, Purified Water, SD Alcohol 39-C, Triethanolamine

PDP

CryoDerm

Pain Relieving Cold Therapy

Gel

Fast Acting, Penetrating Pain Relief For:

Muscle Strains, Joint Pain, Backachke, Arthritis, Sprained Ligaments & Bruises.

Contains Essential Oils and Natural Extracts

MSM Arnica Boswellia Ilex

Active Ingredient: Menthol

32 fl. oz. 1.0L